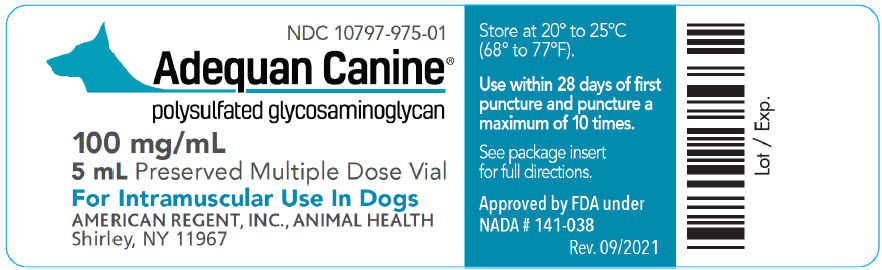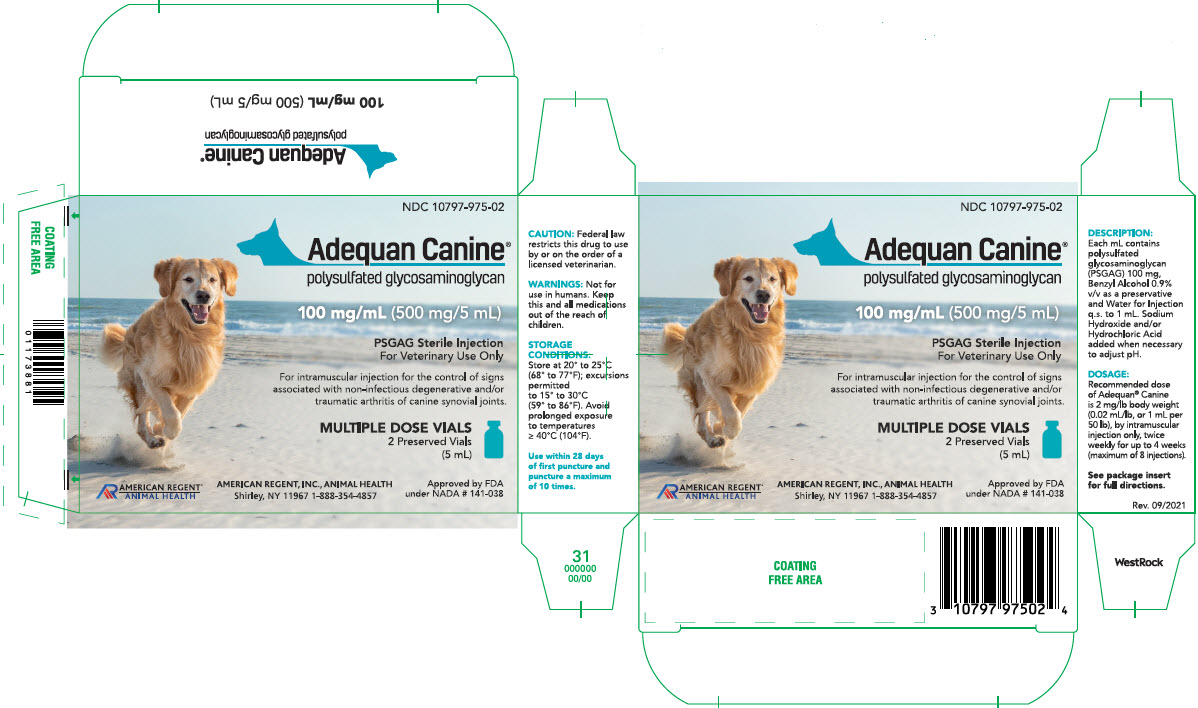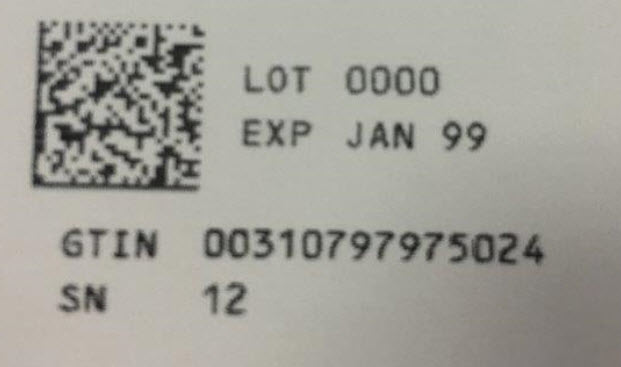 DRUG LABEL: Adequan Canine
NDC: 10797-975 | Form: INJECTION, SOLUTION
Manufacturer: American Regent, Inc.
Category: animal | Type: PRESCRIPTION ANIMAL DRUG LABEL
Date: 20241007

ACTIVE INGREDIENTS: POLYSULFATED GLYCOSAMINOGLYCAN 100 mg/1 mL
INACTIVE INGREDIENTS: BENZYL ALCOHOL; WATER

Adequan® Canine

polysulfated glycosaminoglycan
Solution 100 mg/mL in a 5 mL preserved
Multiple dose vial for intramuscular use in dogs.

Caution:

Federal law restricts this drug to use by or on the order of a licensed veterinarian.

Description:

The active ingredient in Adequan® Canine is polysulfated glycosaminoglycan (PSGAG). Polysulfated glycosaminoglycan is a semi-synthetic glycosaminoglycan prepared by extracting glycosaminoglycans (GAGs) from bovine tracheal cartilage. GAGs are polysaccharides composed of repeating disaccharide units. The GAG present in PSGAG is principally chondroitin sulfate containing 3 to 4 sulfate esters per disaccharide unit. The molecular weight for PSGAG used in the manufacture of Adequan® is 3,000 to 15,000 daltons.

Each mL of Adequan® Canine contains 100 mg of PSGAG, 0.9% v/v benzyl alcohol as a preservative, and water for injection q.s. to 1 mL. Sodium hydroxide and/or hydrochloric acid added when necessary to adjust pH. The solution is clear, colorless to slightly yellow.

Pharmacology:

The specific mechanism of action of Adequan® in canine joints is not known. PSGAG is characterized as a “disease modifying osteoarthritis drug”. Experiments conducted in vitro have shown PSGAG to inhibit certain catabolic enzymes which have increased activity in inflamed joints, and to enhance the activity of some anabolic enzymes. For example, PSGAG has been shown to significantly inhibit serine proteinases. Serine proteinases have been demonstrated to play a role in the Interleukin-l mediated degradation of cartilage proteoglycans and collagen. PSGAG is reported to be an inhibitor of Prostaglandin E2 (PGE2) synthesis. PGE2 has been shown to increase the loss of proteoglycan from cartilage. PSGAG has been reported to inhibit some catabolic enzymes such as elastase, stromelysin, metalloproteases, cathepsin B1, and hyaluronidases, which degrade collagen, proteoglycans, and hyaluronic acid in degenerative joint disease. Anabolic effects studied include ability to stimulate the synthesis of protein, collagen, proteoglycans, and hyaluronic acid in various cells and tissues in vitro. Cultured human and rabbit chondrocytes have shown increased synthesis of proteoglycan and hyaluronic acid in the presence of PSGAG. PSGAGs have shown a specific potentiating effect on hyaluronic acid synthesis by synovial membrane cells in vitro.

Absorption, distribution, metabolism, and excretion of PSGAG following intramuscular injection have been studied in several species, including rats, rabbits, humans, horses and dogs.

Studies in rabbits showed maximum blood concentrations of PSGAG following IM injection were reached between 20 to 40 minutes following injection, and that the drug was distributed to all tissues studied, including articular cartilage, synovial fluid, adrenals, thyroid, peritoneal fluid, lungs, eyes, spinal cord, kidneys, brain, liver, spleen, bone marrow, skin, and heart.

Following intramuscular injection of PSGAG in humans, the drug was found to be bound to serum proteins. PSGAG binds to both albumin and chi- and beta-globulins and the extent of the binding is suggested to be 30 to 40%. Therefore, the drug may be present in both bound and free form in the bloodstream. Because of its relatively low molecular weight, the synovial membrane is not a significant barrier to distribution of PSGAG from the bloodstream to the synovial fluid. Distribution from the synovial fluid to the cartilage takes place by diffusion. In the articular cartilage the drug is deposited into the cartilage matrix.

Serum and synovial fluid distribution curves of PSGAG have been studied in dogs and appear similar to those found in humans and rabbits.

In rabbits, metabolism of PSGAG is reported to take place in the liver, spleen, and bone marrow. Metabolism may also occur in the kidneys. PSGAG administered intramuscularly and not protein bound or bound to other tissues is excreted primarily via the kidneys, with a small proportion excreted in the feces.

Toxicity:

In a subacute toxicity study, 32 adult beagle dogs (4 males and 4 females per treatment group) received either 0.9% saline solution or PSGAG at a dose of 5 mg, 15 mg, or 50 mg per kg of body weight (approximately 2.3, 6.8, or 22.7 mg/lb), via intramuscular injection twice weekly for 13 weeks. PSGAG doses represent approximately 1X, 3X, and 10X the recommended dosage of 2 mg/lb, and more than 3 times the recommended 4-week duration of treatment. Necropsies were performed 24 hours after the final treatment. During week 12, one dog in the 50 mg/kg dosage group developed a large hematoma at the injection site which necessitated euthanasia. No other mortalities occurred during the treatment period. Statistically significant changes in the 50 mg/kg group included increased prothrombin time, reduced platelet count, an increase in ALT and cholesterol, and increased liver and kidney weights. Increased cholesterol and kidney weights were also noted in the 15 mg/kg group. Microscopic lesions were noted in the liver (Kupffer cells containing eosinophilic foamy cytoplasm), kidneys (swollen, foamy cells in the proximal convoluted tubules), and lymph nodes (macrophages with eosinophilic foamy cytoplasm) in the 15 mg/kg and 50 mg/kg groups. Intramuscular inflammation, hemorrhage, and degeneration were seen in all 3 PSGAG treated groups; the incidence and severity appeared dose related.

Efficacy:

Efficacy of Adequan® Canine was demonstrated in two studies. A laboratory study using radiolabeled PSGAG established distribution of PSGAG into canine serum and synovial fluid following a single intramuscular injection of 2 mg/lb. A clinical field trial was conducted in dogs diagnosed with radiographically-confirmed traumatic and/or degenerative joint disease of 1 or 2 joints. Joints evaluated included hips, stifles, shoulders, hocks and elbows. Fifty-one dogs were randomly assigned to receive either Adequan® Canine at 2 mg/lb of body weight or 0.9% saline. Both treatments were administered by intramuscular injection twice weekly for 4 weeks (8 injections total). Investigators administering treatment and evaluating the dogs were unaware of the treatment assignment. A total of 71 limbs in 51 dogs were evaluated. Of these, 35 limbs in 24 dogs were in the Adequan® Canine treated group. Each lame limb was scored for lameness at a walk, lameness at a trot, pain, range of motion, and functional disability. The scores for the individual parameters were combined to determine a total orthopedic score. At the end of the treatment period, dogs treated with Adequan® Canine showed a statistically significant improvement in range of motion and total orthopedic score over placebo treated control dogs.

Indications and Usage:

Adequan® Canine is recommended for intramuscular injection for the control of signs associated with non-infectious degenerative and/or traumatic arthritis of canine synovial joints.

Contraindications:

Do not use in dogs showing hypersensitivity to PSGAG. PSGAG is a synthetic heparinoid; do not use in dogs with known or suspected bleeding disorders.

Precautions:

The safe use of Adequan® Canine used in breeding, pregnant, or lactating dogs has not been evaluated. Use with caution in dogs with renal or hepatic impairment.

Adverse Reactions:

In the clinical efficacy trial, 24 dogs were treated with Adequan® Canine twice weekly for 4 weeks. Possible adverse reactions were reported after 2.1% of the injections. These included transient pain at the injection site (1 incident), transient diarrhea (1 incident each in 2 dogs), and abnormal bleeding (1 incident). These effects were mild and self-limiting and did not require interruption of therapy.

Post Approval Experience (2014)

The following adverse events are based on voluntary, post-approval reporting. Not all adverse reactions are reported to FDA/CVM. It is not always possible to reliably estimate the adverse event frequency or establish a causal relationship to product exposure using these data. The signs reported are listed in decreasing order of reporting frequency.

Vomiting, anorexia, depression/lethargy, diarrhea.

In some cases, death has been reported.

To report suspected adverse drug events, contact American Regent, Inc. at 1-888-354-4857. For additional information about adverse drug experience reporting for animal drugs, contact FDA at 1-888-FDA-VETS or http://www.fda.gov/AnimalVeterinary/SafetyHealth.

Warnings:

Not for use in humans. Keep this and all medications out of reach of children.

Dosage and Administration:

Practice aseptic techniques in withdrawing each dose to decrease the possibility of post-injection bacterial infections. Adequately clean and disinfect the stopper prior to entry with a sterile needle and syringe. Use only sterile needles, and use each needle only once.

The vial stopper may be punctured a maximum of 10 times.

The recommended dose of Adequan® Canine is 2 mg/lb body weight (.02 mL/lb, or 1 mL per 50 lb), by intramuscular injection only, twice weekly for up to 4 weeks (maximum of 8 injections). Do not exceed the recommended dose or therapeutic regimen. Do not mix Adequan® Canine with other drugs or solvents.

Storage Conditions:

Store at 20° to 25°C (68° to 77°F) excursions permitted to 15° to 30°C (59° to 86°F) (See USP Controlled Room Temperature). Avoid prolonged exposure to temperatures ≥ 40°C (104°F).

Use within 28 days of first puncture and puncture a maximum of 10 times. Dispose of spent needles in accordance with all federal, state and local environmental laws.

How Supplied:

Adequan® Canine Solution 100 mg/mL in a 5 mL preserved multiple dose vial.

NDC 10797-975-02 5 mL Multiple Dose Vials Packaged 2 vials per box
AMERICAN REGENT, INC.
ANIMAL HEALTH
Shirley, NY 11967
(1-888-354-4857)
Approved by FDA under NADA # 141-038

Made in U.S.A.
Rev. 9/2021
IN975
MG #44454

Package Label.Principal Display Panel - Container

NDC 10797-975-01

Adequan® Canine
polysulfated glycosaminoglycan
100 mg/mL
5 mL Preserved Multiple Dose Vial
For Intramuscular Use in Dogs
Store at 20° to 25°C (68° to 77°F).
Use within 28 days of first puncture and puncture a maximum of 10 times.
See package insert for full directions.
AMERICAN REGENT, INC., ANIMAL HEALTH
Shirley, NY 11967

Approved by FDA under NADA # 141-038

Rev. 09/2021

Package Label.Principal Display Panel - Carton

NDC 10797-975-02
Adequan® Canine
polysulfated glycosaminoglycan
100 mg/mL (500 mg/5 mL)
PSGAG Sterile Injection
For Veterinary Use Only
For intramuscular injection for the control of signs associated with non-infectious degenerative and/or traumatic arthritis of canine synovial joints.
MULTIPLE DOSE VIALS
2 Preserved Vials
(5 mL)
AMERICAN REGENT, INC., ANIMAL HEALTH
Shirley, NY 11967
1-888-354-4857
Approved by FDA under NADA # 141-038